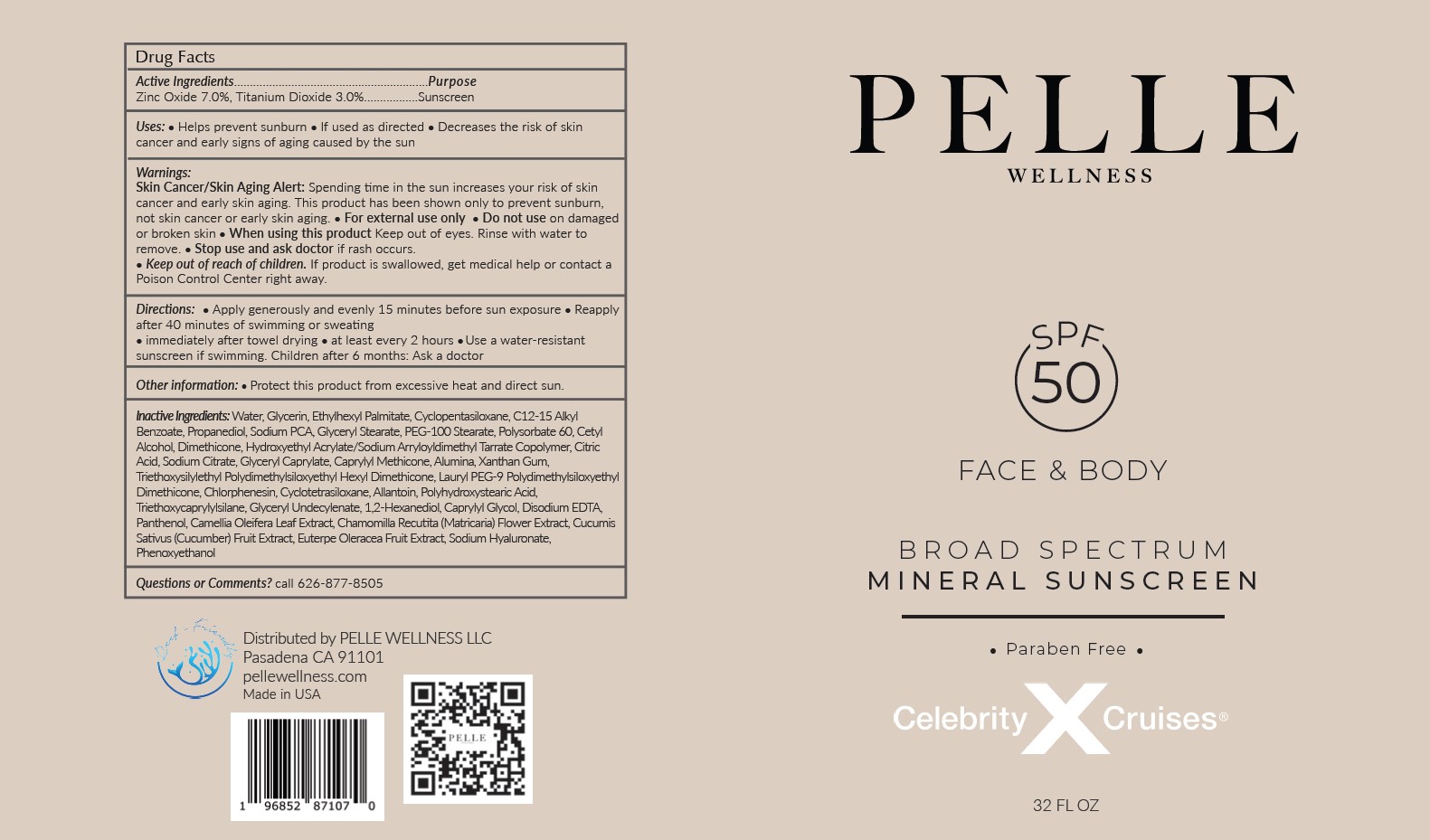 DRUG LABEL: PELLE WELLNESS SPF 50 FACE AND BODY BROAD SPECTRUM MINERAL SUNSCREEN
NDC: 83625-101 | Form: CREAM
Manufacturer: Pelle Wellness LLC
Category: otc | Type: HUMAN OTC DRUG LABEL
Date: 20230826

ACTIVE INGREDIENTS: TITANIUM DIOXIDE 3 g/100 mL; ZINC OXIDE 7 g/100 mL
INACTIVE INGREDIENTS: DIMETHICONE; CAPRYLYL TRISILOXANE; CYCLOMETHICONE 4; MATRICARIA CHAMOMILLA FLOWERING TOP; ETHYLHEXYL PALMITATE; SODIUM PYRROLIDONE CARBOXYLATE; GLYCERYL CAPRYLATE; ALUMINUM OXIDE; HYALURONATE SODIUM; PHENOXYETHANOL; WATER; GLYCERIN; CYCLOMETHICONE 5; ALKYL (C12-15) BENZOATE; PROPANEDIOL; GLYCERYL MONOSTEARATE; PEG-100 STEARATE; POLYSORBATE 60; CETYL ALCOHOL; HYDROXYETHYL ACRYLATE/SODIUM ACRYLOYLDIMETHYL TAURATE COPOLYMER (45000 MPA.S AT 1%); CITRIC ACID MONOHYDRATE; SODIUM CITRATE; XANTHAN GUM; TRIETHOXYSILYLETHYL POLYDIMETHYLSILOXYETHYL HEXYL DIMETHICONE; LAURYL PEG-9 POLYDIMETHYLSILOXYETHYL DIMETHICONE; CHLORPHENESIN; ALLANTOIN; POLYHYDROXYSTEARIC ACID (2300 MW); TRIETHOXYCAPRYLYLSILANE; GLYCERYL 1-UNDECYLENATE; 1,2-HEXANEDIOL; CAPRYLYL GLYCOL; EDETATE DISODIUM ANHYDROUS; PANTHENOL; CAMELLIA OLEIFERA LEAF; CUCUMIS SATIVUS WHOLE; EUTERPE OLERACEA WHOLE

Pelle Wellness (as PLD) - Face & Body Sunscreen SPF-50 (83625-101)

ACTIVE INGREDIENTS

ZINC OXIDE 7.0%

TITANIUM DIOXIDE 3.0%

PURPOSE

SUNSCREEN

USES

- Helps prevent sunburn
- If used as directed
- Decreases the risk of skin cancer and early signs of aging caused by the sun

WARNINGS

Skin Cancer/Skin Aging Alert: Spending time in the sun increases your risk of skin cancer and early skin aging. This product has been shown only to prevent sunburn, not skin cancer or early skin aging.

- For external use only
- Do not use on damaged or broken skin
- When using this product Keep out of eyes. Rinse with water to remove.
- Stop use and ask doctor if rash occurs.

- Keep out of reach of children. If product is swallowed, get medical help or contact a Poison Control Center right away.

DIRECTIONS

- Apply generously and evenly 15 minutes before sun exposure
- Reapply after 40 minutes of swimming or sweating
- immediately after towel drying
- at least every 2 hours
- Use a water-resistant sunscreen if swimming.

Children after 6 months: Ask a doctor

STORAGE AND HANDLING

- Protect this product from excessive heat and direct sun.

INACTIVE INGREDIENTS

Water, Glycerin, Ethylhexyl Palmitate, Cyclopentasiloxane, C12-15 Alkyl Benzoate, Propanediol, Sodium PCA, Glyceryl Stearate, PEG-100 Stearate, Polysorbate 60, Cetyl Alcohol, Dimethicone, Hydroxyethyl Acrylate/Sodium Acryloyldimethyl Taurate Copolymer, Citric
Acid, Sodium Citrate, Glyceryl Caprylate, Caprylyl Methicone, Alumina, Xanthan Gum, Triethoxysilylethyl Polydimethylsiloxyethyl Hexyl Dimethicone, Lauryl PEG-9 Polydimethylsiloxyethyl Dimethicone, Chlorphenesin, Cyclotetrasiloxane, Allantoin, Polyhydroxystearic Acid,
Triethoxycaprylylsilane, Glyceryl Undecylenate, 1,2-Hexanediol, Caprylyl Glycol, Disodium EDTA, Panthenol, Camellia Oleifera Leaf Extract, Chamomilla Recutita (Matricaria) Flower Extract, Cucumis Sativus (Cucumber) Fruit Extract, Euterpe Oleracea Fruit Extract, Sodium Hyaluronate, Phenoxyethanol

Questions or Comments?

call 626-877-8505